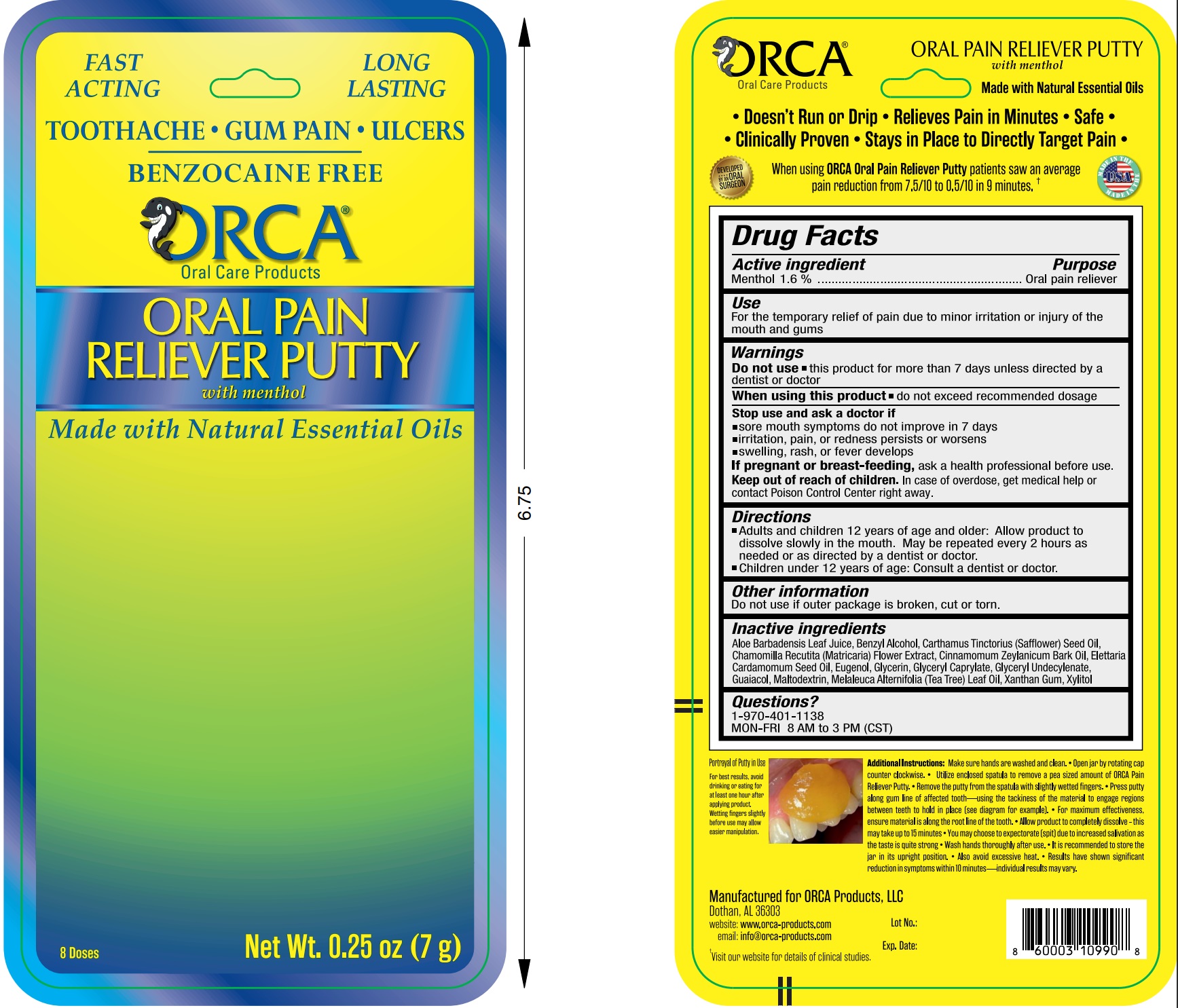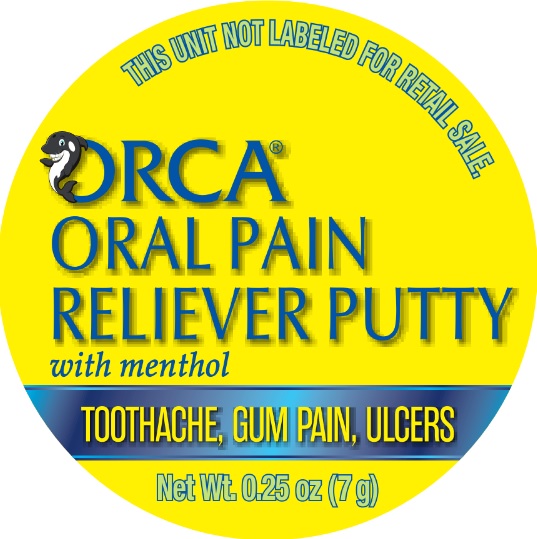 DRUG LABEL: ORCA Pain Reliever Putty with Menthol
NDC: 82939-001 | Form: PASTE
Manufacturer: ORCA Products, LLC
Category: otc | Type: HUMAN OTC DRUG LABEL
Date: 20231110

ACTIVE INGREDIENTS: MENTHOL, UNSPECIFIED FORM 8.4 mg/0.525 g
INACTIVE INGREDIENTS: CARDAMOM OIL; CHAMOMILE; CINNAMON OIL; CLOVE OIL; GLYCERIN; GUAIACOL; MALTODEXTRIN; SAFFLOWER OIL; TEA TREE OIL; XANTHAN GUM; XYLITOL; ALOE VERA LEAF

ORCA Pain Reliever Putty with Menthol

Active ingredient

Menthol 1.6%

Purpose

oral pain reliever

Use

- for the temporary relief of pain due to minor irritation or injury of the mouth and gums

Warnings

Do not use

- this product for more than 7 days unless directed by a dentist or doctor.

When using this product

- do not exceed recommended dosage.

Stop use and ask a doctor if

- sore mouth symptoms do not improve in 7 days
- irritation, pain, or redness persists or worsens
- swelling, rash, or fever develops

If pregnant or breast-feeding,

ask a health professional before use.

Keep out of reach of children.

In case of overdose, get medical help or contact Poison Control Center right away.

Directions

- Adults and children 12 years of age and older: Allow product dissolve slowly in the mouth. May be repeated every 2 hours as needed or as directed by a dentist or doctor

- Children under 12 years of age: Consult a dentist or doctor.

Other information

- Do not use if outer package is broken, cut or torn.

Inactive ingredients

Aloe Barbadensis Leaf Juice, Benzyl Alcohol, Carthamus Tinctorius (Safflower) Seed Oil, Chamomilla Recutita (Matricaria) Flower Extract, Cinnamomum Zeylanicum Bark Oil, Elettaria Cardamomum Seed Oil, Eugenol, Glycerin, Glyceryl Caprylate, Glyceryl Undecylenate, Guaiacol, Maltodextrin, Melaleuca Alternifolia (Tea Tree) Leaf Oil, Xanthan Gum, Xylitol

Questions?

1-970-401-1138 MON-FRI 8 AM to 3 PM (CST)